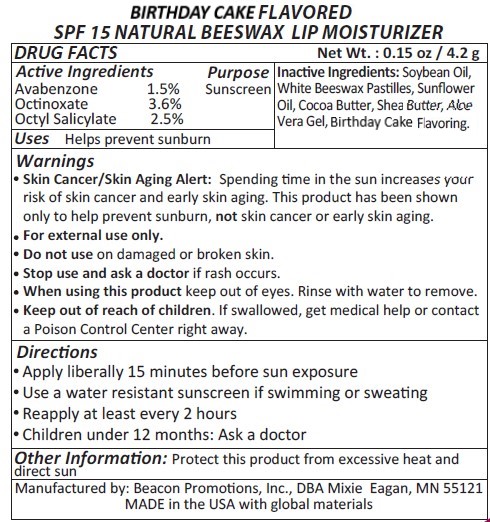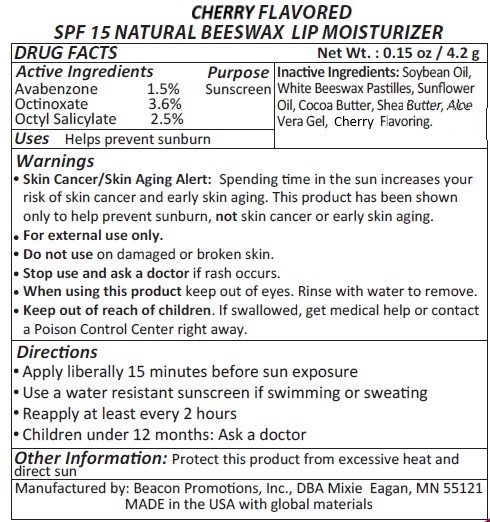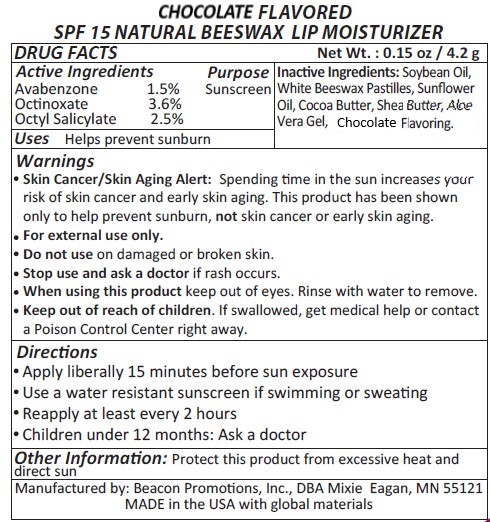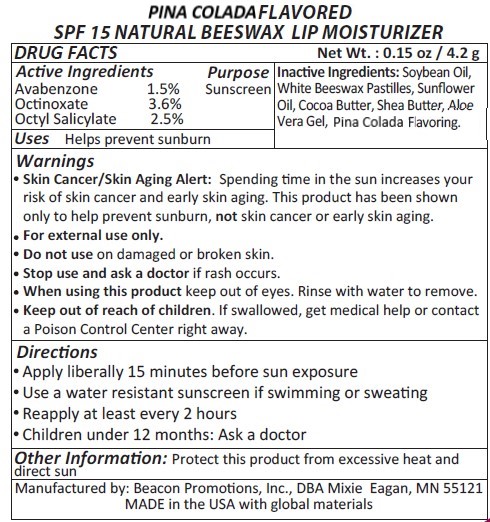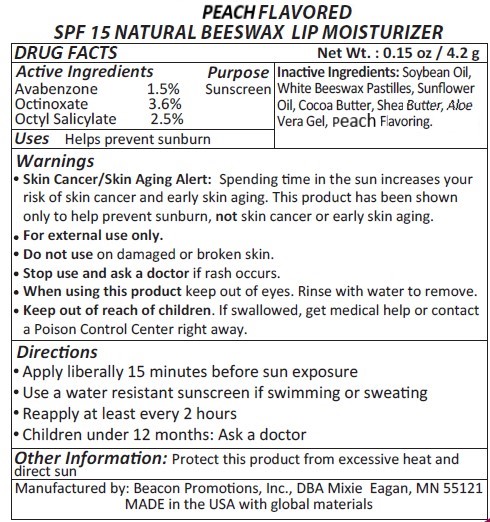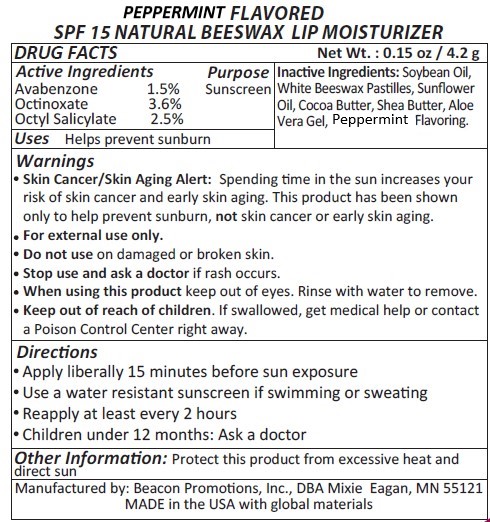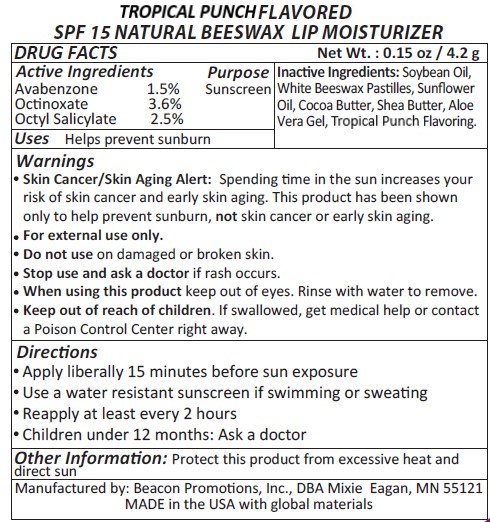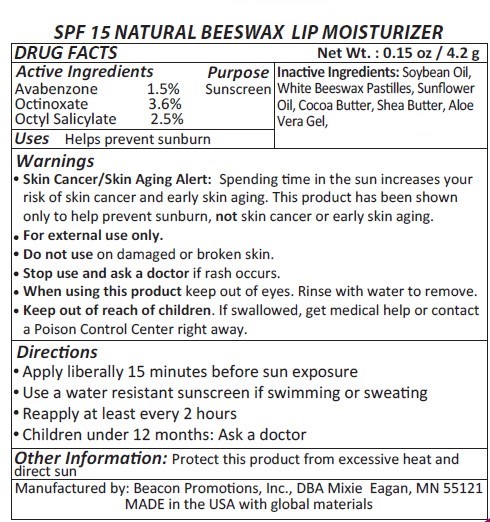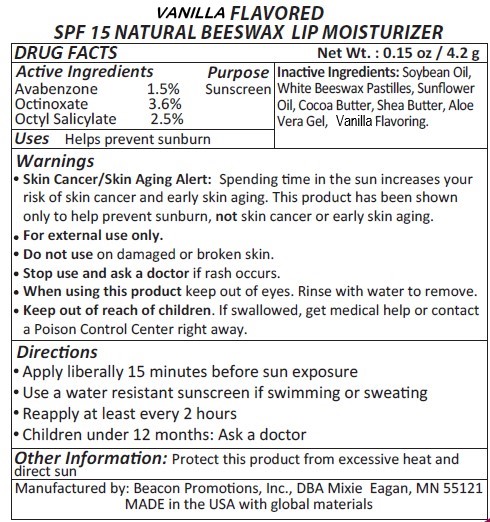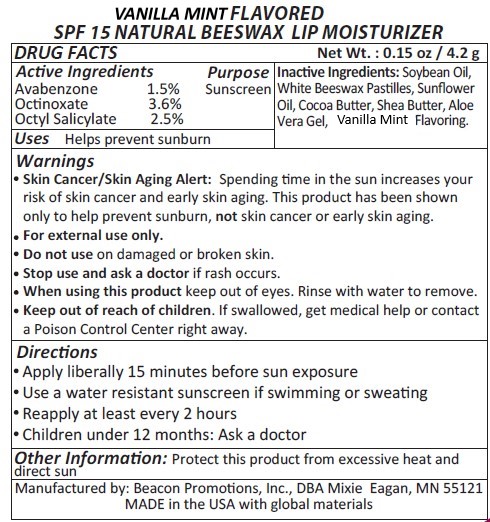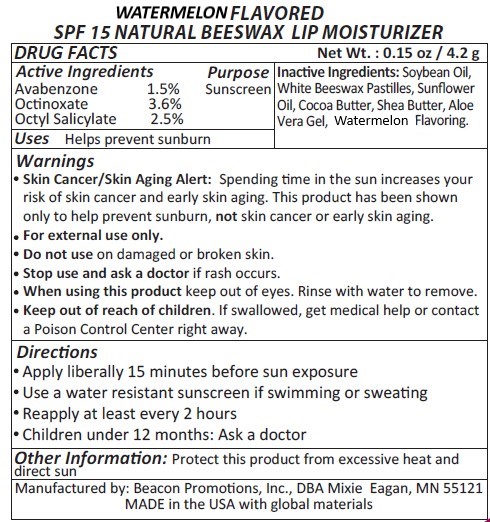 DRUG LABEL: LB60-Vanilla
NDC: 70445-304 | Form: LIPSTICK
Manufacturer: Beacon Promotions Inc.
Category: otc | Type: HUMAN OTC DRUG LABEL
Date: 20240103

ACTIVE INGREDIENTS: OCTINOXATE 3.6 g/100 g; OCTISALATE 2.5 g/100 g; AVOBENZONE 1.5 g/100 g
INACTIVE INGREDIENTS: SAFFLOWER OIL; ALOE; SOYBEAN OIL; SHEA BUTTER; COCOA BUTTER; SUNFLOWER OIL; WHITE WAX

SPF 15 Lip Moisturizer

Active Ingredients

Octinoxate 3.6%

Octisalate 2.5%

Avobenzone 1.5%

Inactive Ingredient

Hydrogenated Soybean Oil, Sunflower Oil, Yellow Bees Wax Pearls, Cocoa Butter, Shea Butter, Vitamin E, Aloe Vera Gel, Flavoring

Directions

Apply liberally 15 minutes before sun exposure

Use a water resistant sunscreen if swimming or sweating

Reapply every 2 hours

Children under 6 months : Ask a doctor

Warnings

Skin Cancer/Skin Aging Alert: Spending too much time in the sun increases your risk of skin cancer and early skin aging. This product has been shown to only help prevent sunburn, not skin cancer or early skin aging.

For external use only.

Do not use on damaged or broken skin.

Stop use and ask doctor if rash occurs.

When using this product keep out of eyes.

Keep out of reach of children. If swallowed get medical help or contact posion control center right away.

Keep out of reach of children.

DOSAGE AND ADMINISTRATION

Avabenzone 1.5%
Oc􀆟noxate 3.6%
Octyl Salicylate 2.5%

Apply liberally 15 minutes before sun exposure

Purpose

Sunscreen

PURPOSE

Sunscreen